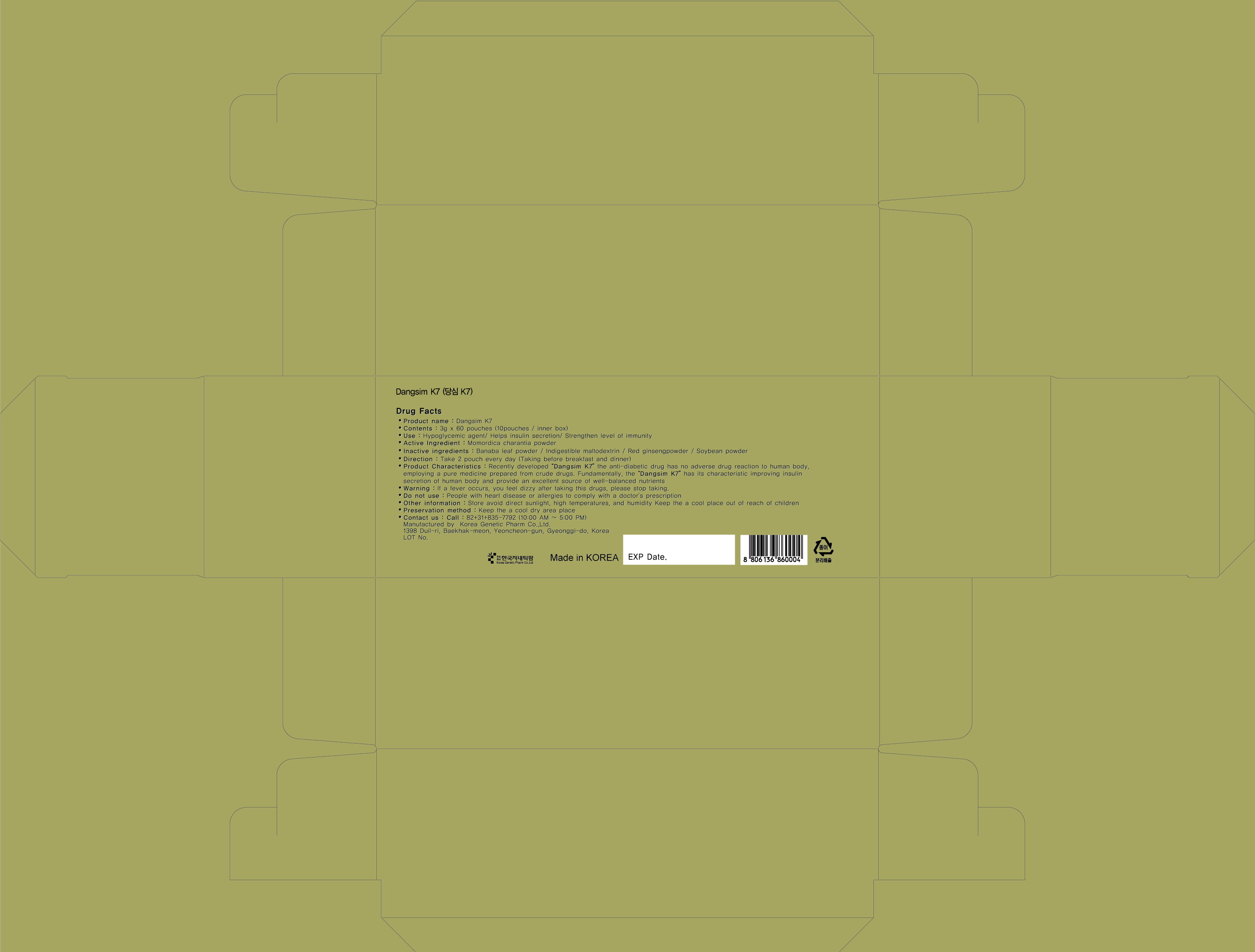 DRUG LABEL: Dangsim K-7
NDC: 42707-1001 | Form: GRANULE
Manufacturer: Korea Genetic Pharm Co., Ltd 
Category: otc | Type: HUMAN OTC DRUG LABEL
Date: 20120215

ACTIVE INGREDIENTS: MOMORDICA CHARANTIA FRUIT 13 g/100 g
INACTIVE INGREDIENTS: MALTODEXTRIN; PANAX GINSENG FRUIT; SOYBEAN

Drug Facts

active ingredient: momordica charantia powder

INACTIVE INGREDIENT

banaba leaf powder, indigestible maltodextrin, red ginseng powder, soybean powder

PURPOSE

hypoglycemic agent / helps insulin secretion / strengthen level of immunity

keep out of reach of the children

INDICATIONS AND USAGE

take 2 pouch every day (taking before breakfast and dinner)

WARNINGS

if a fever occurs or you feel dizzy after taking this drugs, immediately stop taking

DOSAGE AND ADMINISTRATION

do not take if you have heart disease